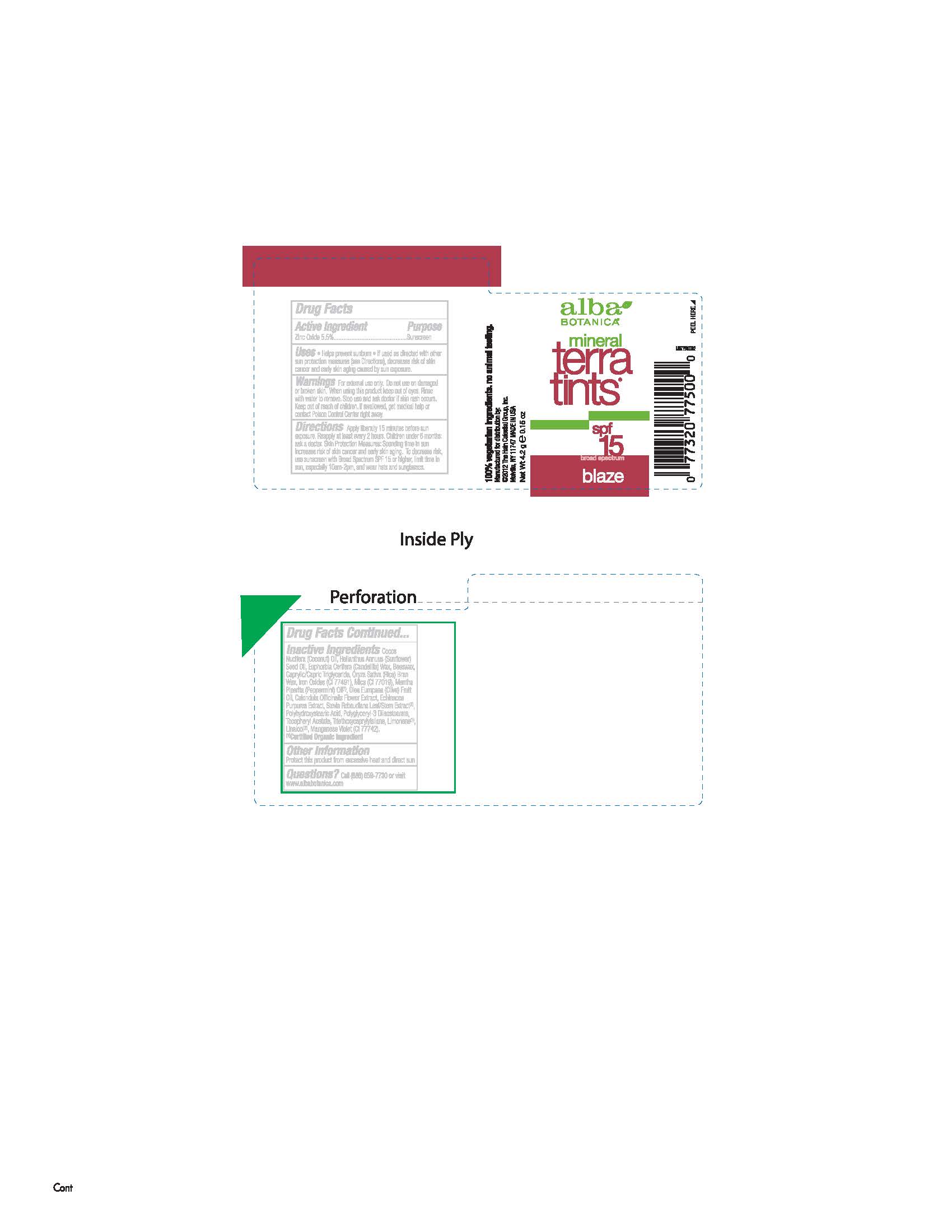 DRUG LABEL: Alba Mineral Terra Tint SPF15 Blaze
NDC: 61995-2500 | Form: CREAM
Manufacturer: The Hain Celestial Group, Inc.
Category: otc | Type: HUMAN OTC DRUG LABEL
Date: 20140922

ACTIVE INGREDIENTS: ZINC OXIDE 5.5 g/100 g
INACTIVE INGREDIENTS: COCONUT OIL; CANDELILLA WAX; YELLOW WAX; RICE BRAN; FERRIC OXIDE RED; MICA; OLIVE OIL; CALENDULA OFFICINALIS FLOWER; ECHINACEA PURPUREA ROOT; STEVIA REBAUDIUNA LEAF; POLYHYDROXYSTEARIC ACID (2300 MW); POLYGLYCERYL-3 DIISOSTEARATE; SUNFLOWER OIL; PEPPERMINT OIL; TRIETHOXYCAPRYLYLSILANE; MEDIUM-CHAIN TRIGLYCERIDES; MANGANESE VIOLET; .ALPHA.-TOCOPHEROL ACETATE

Active Ingredient

Zinc Oxide 5.5%

DOSAGE AND ADMINISTRATION

Cream. Apply liberally 15 minutes before sun exposure

PURPOSE

Sunscreen

WARNINGS

For external use only. Do not use on damaged skin. When using this product keep out of eyes.

INDICATIONS AND USAGE

Helps prevents sunburns. If uses as directed with other sun protection measures, decreases risk of skin cancer and early skin aging caused by sun exposure

Keep out of reach of children. If swallowed get medical help right away or contact Poison Center right away.

INACTIVE INGREDIENT

Cocus Nucifera (Coconut) Oil, Helianthus Annuus (Sunflower) Seed Oil, Euphorbia Cerifera (Candelilla) Wax, Iron Oxides (CI 77491), Mica (CI 77019), Mentha Piperita (Peppermint) Oil (1), Olea Europaea (Olive) Fruit Oil, Calendula Officinalis Flower Extract, Echinacea Purpurea Extract, Stevia Rebaudiana Leaf/Stem Extract (1), Polyhydroxystearic Acid, Polyglyceryl-3 Diisostearate, Tocopheryl Acetate, Triethoxycaprylylsilane, Limonene, Linalool.

(1) Certified Organicf Ingredient